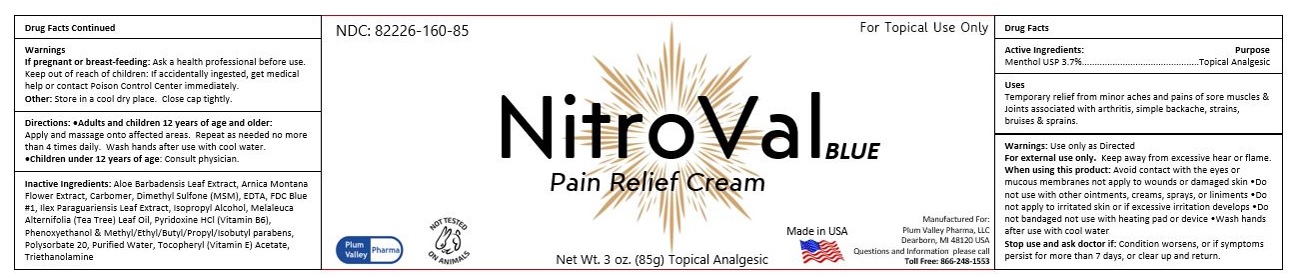 DRUG LABEL: NitroVal Blue
NDC: 82226-160 | Form: CREAM
Manufacturer: PLUM VALLEYPHARMA LLC
Category: otc | Type: HUMAN OTC DRUG LABEL
Date: 20220621

ACTIVE INGREDIENTS: MENTHOL 3.7 g/100 g
INACTIVE INGREDIENTS: ILEX PARAGUARIENSIS LEAF; ISOPROPYL ALCOHOL; 2-(2-(2-(2-PHENOXYETHOXY)ETHOXY)ETHOXY)ETHANOL; WATER; CARBOMER INTERPOLYMER TYPE A (ALLYL SUCROSE CROSSLINKED); PROPYLPARABEN; POLYSORBATE 20; .ALPHA.-TOCOPHEROL ACETATE, D-; TROLAMINE; ISOBUTYLPARABEN; ALOE VERA LEAF; ARNICA MONTANA FLOWER; EDETATE DISODIUM; MELALEUCA ALTERNIFOLIA LEAF; DIMETHYL SULFONE; PYRIDOXINE HYDROCHLORIDE; METHYLPARABEN; ETHYLPARABEN; BUTYLPARABEN

NitroVal Blue cream

Active ingredients:

Menthol USP 3.7%

Purpose

Topical analgesic

INDICATIONS AND USAGE

Uses Temporary relief from minor aches and pains of sore muscles & Joints associated with arthritis, simple backache, strains, bruises & sprains.

Warnings

For external use only. Keep away from excessive hear or flame.

When using this product

- Avoid contact with the eyes or mucous membranes not apply to wounds or damaged skin.
- Do not use with other ointments, creams, sprays, or liniments
- Do not apply to irritated skin or if excessive irritation develops
- Do not bandaged not use with heating pad or device
- Wash hands after use with cool water

Stop use and ask a doctor if

Condition worsens, or if symptoms persist for more than 7 days, or clear up and return.

Warnings
If pregnant or breast-feeding: Ask a health professional before use.
Keep out of reach of children: If accidentally ingested, get medical
help or contact Poison Control Center immediately.
Other: Store in a cool dry place. Close cap tightly.

Directions:

- Adults and children 12 years of age and older:
  Apply and massage onto affected areas. Repeat as needed no more
  than 4 times daily. Wash hands after use with cool water.
- Children under 12 years of age: Consult physician.

Inactive Ingredients: Aloe Barbadensis Leaf Extract, Arnica Montana
Flower Extract, Carbomer, Dimethyl Sulfone (MSM), EDTA, FDC Blue
#1, ilex Paraguariensis Leaf Extract, Isopropyl Alcohol, Melaleuca
Alternifolia (Tea Tree) Leaf Oil, Pyridoxine HCl (Vitamin B6),
Phenoxyethanol & Methyl/Ethyl/Butyl/Propyl/Isobutyl parabens,
Polysorbate 20, Purified Water, Tocopheryl (Vitamin E) Acetate,
Triethanolamine

Manufactured For:
Plum Valley Pharma, LLC
Dear born, MI 48120 USA
Questions and Information please call
Toll Free: 866-248-1553

PACKAGE LABEL

NDC: 82226-160-85 For Topical Use Only

NitroValBLUE

Pain Relief Cream

Plum
Valley Pharma

Net Wt. 3 oz. (85g) Topical Analgesic

Made in USA

Manufactured For:
Plum Valley Pharma, LLC
Dear born, MI 48120 USA
Questions and Information please call
Toll Free: 866-248-1553